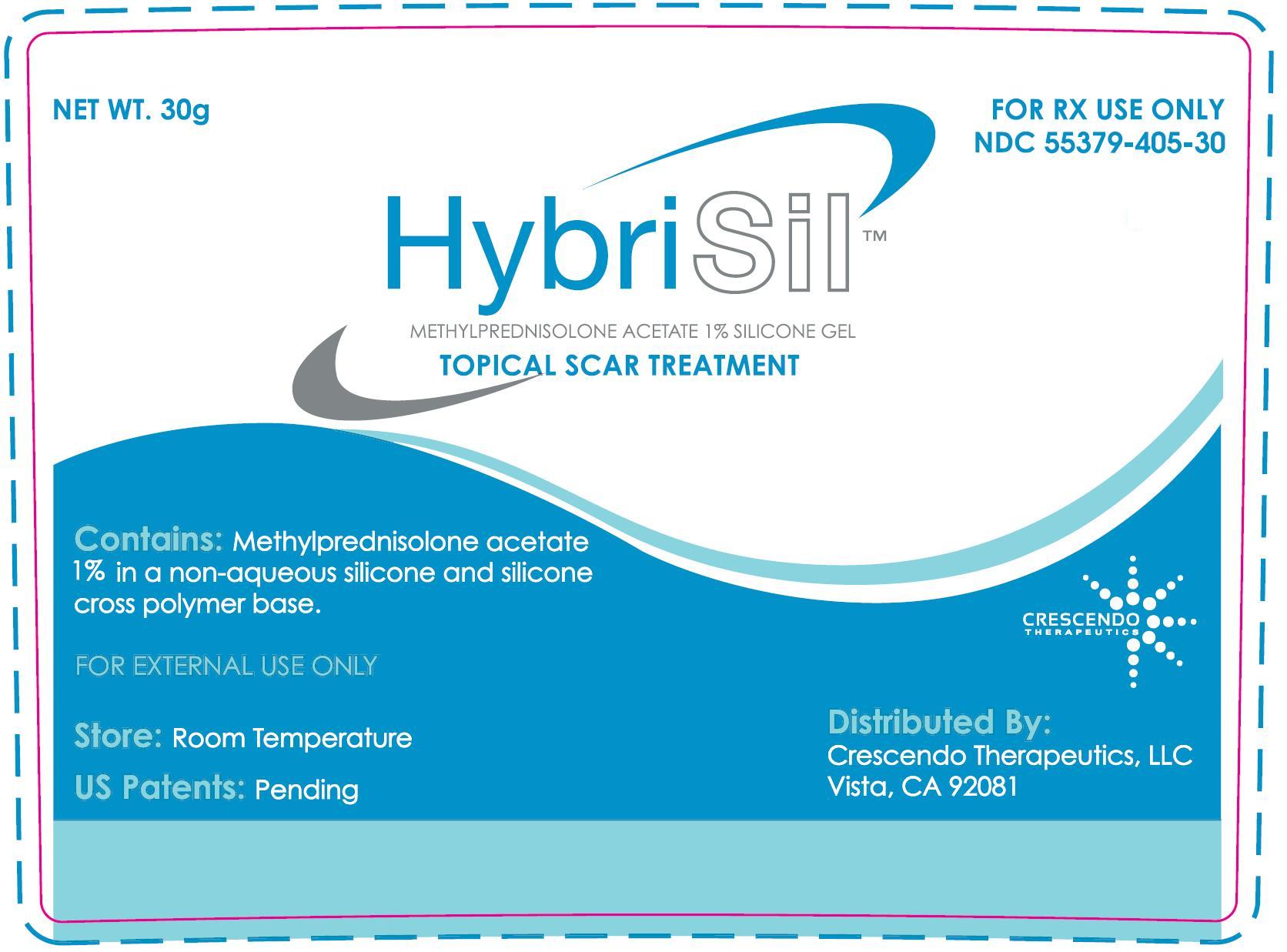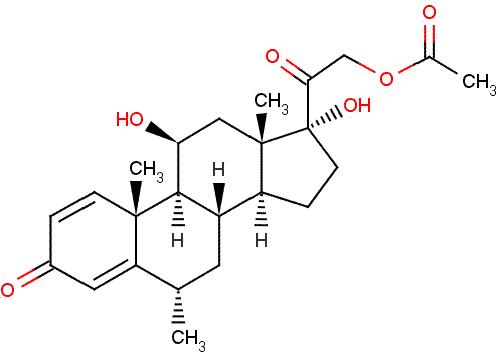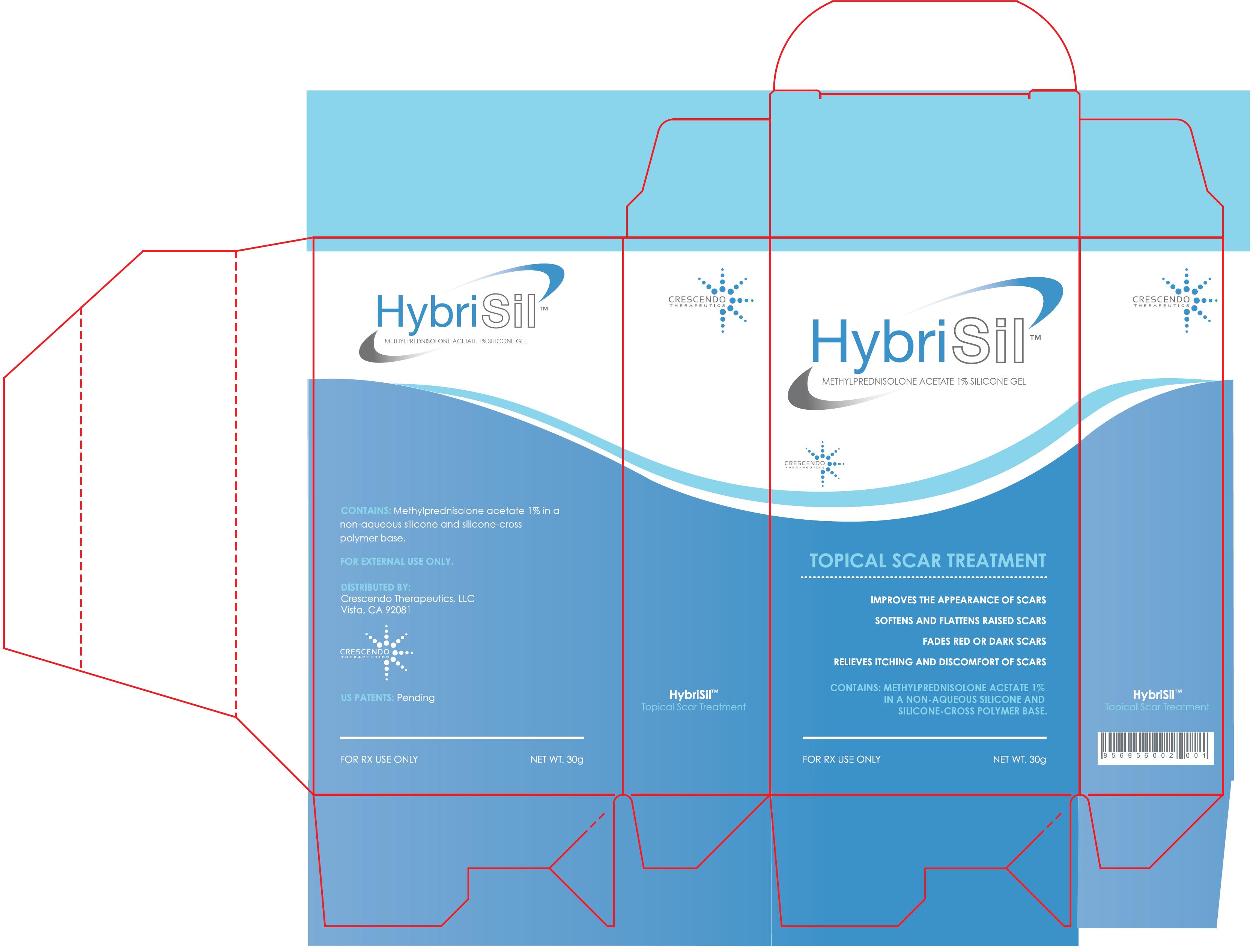 DRUG LABEL: Hybrisil
NDC: 55379-405 | Form: GEL
Manufacturer: BioZone Laboratories, Inc.
Category: prescription | Type: HUMAN PRESCRIPTION DRUG LABEL
Date: 20110422

ACTIVE INGREDIENTS: Methylprednisolone Acetate 10 mg/1 g

DESCRIPTION

DESCRIPTION: The topical corticosteroids constitute a class of primary synthetic steroids used as anti-inflammatory and anti-pruritic agents. HybriSil™ Topical Silicone Gel contains methylprednisolone acetate, USP (CAS 53-36-1)
Chemical Name: Pregna-1,4-diene-3,20-dione, 21-(acetyloxy)-11,17-dihydroxy-6-methyl-,(6α,11ß)-,11ß,17,21-Trihydroxy-6α-methylpregna-1,4-diene-3,20-dione 21-acetate. It has a molecular formula of C24H32O6 and a molecular weight of 416.51.

Contains: Methylprednisolone acetate 1.0% in a base of: silicone cross-polymers, alcohol, cyclomethicones, propylene glycol, PEG-12 glyceryl dimyristate, and benzyl alcohol.

CLINICAL PHARMACOLOGY

Topical corticosteroids share anti-inflammatory, anti-pruritic and vasoconstrictive actions.
The mechanism of anti-inflammatory activity of the topical corticosteroids is unclear. Various laboratory methods, including vasoconstriction assays are used to compare and predict potencies and or clinical efficacies of the topical corticosteroids. There is some evidence to suggest that a recognizable correlation exists between vasoconstrictive potency and therapeutic efficacy in man.

Pharmacokinetics

The extent of percutaneous absorption of topical corticosteroids is determined by many factors including the vehicle, the integrity of the epidermal barrier and the use of occlusive dressings.
Topical corticosteroids can be absorbed from normal intact skin. Inflammation and /or other diseases processes in the skin increase percutaneous absorption. Occlusive dressings substantially increase the percutaneous absorption of topical corticosteroids. Thus, occlusive dressings may be a valuable therapeutic adjunct for treatment of resistant dermatoses. (see DOSAGE AND ADMINISTRATION)
Once absorbed through the skin, topical corticosteroids are handled through pharmacokinetic pathways similar to systemically administered corticosteroids. Corticosteroids are bound to plasma proteins in varying degrees. Corticosteroids are metabolized primarily in the liver and are then excreted by the kidneys. Some of the topical corticosteroids and their metabolites are also excreted into the bile.

INDICATIONS AND USAGE

HybriSil™ topical gel is indicated for the relief of the inflammatory and pruritic manifestations of corticosteroid responsive dermatoses, including those associated with the formation of scar tissue.

CONTRAINDICATIONS

Topical corticosteroids are contraindicated in those patients with a history of hypersensitivity to any of the components of the preparation.

PRECAUTIONS

General: Systemic absorption of topical corticosteroids has produced reversible hypothalamic-pituitary-adrenal (HPA) axis suppression, manifestations of Cushing’s syndrome, hyperglycemia and glucosuria in some patients.
Conditions which augment systemic absorption include the application of more potent steroid use over large surface areas, prolonged use and addition of occlusive dressings.
Therefore, patients receiving a large dose of a potent topical steroid applied to a large surface area or under an occlusive dressing should be evaluated periodically for evidence of HPA axis suppression by using the urinary free cortisol and ACTH stimulation tests. If HPA axis suppression is noted, an attempt should be made to withdraw the drug, to reduce the frequency of applications, or to substitute a less potent steroid.
Recovery of HPA axis function is generally prompt and complete upon discontinuation of the drug. Infrequently, signs and symptoms of steroid withdrawal may occur, requiring supplemental systemic corticosteroids.
Children may absorb proportionately larger amounts of topical corticosteroids and thus be more susceptible to systemic toxicity. (See PRECAUTIONS-Pediatric Use)
This medication contains alcohol. It may produce irritation or burning sensations on open lesions. If irritation develops, topical corticosteroids should be discontinued and appropriate therapy instituted.
As with any topical corticosteroid product, prolonged use may produce atrophy of the skin and subcutaneous tissues. When used on intertriginous or flexor areas, or on the face, this may occur even with short-term use.
In the presence of dermatological infections, the use of an appropriate antifungal or antibacterial agent should be instituted. If a favorable response does not occur promptly, the corticosteroid should be discontinued until the infection has been adequately controlled.

Information for the Patient

Patients using topical corticosteroids should receive the following information and instructions:
1. This medication is to be used as directed by the physician. It is for external use only. Avoid contact with the eyes.
2. Patients should be advised not to use this medication for any disorder other than for which it is prescribed.
3. Treated skin areas should not be bandaged or otherwise covered or wrapped as to be occlusive unless directed by the physician.
4. Patients should report any signs of local adverse reactions, especially under occlusive dressing.
5. Parents of pediatric patients should be advised not to use tight-fitting diapers or plastic pants on a child being treated in the diaper area as these garments may constitute occlusive dressings.

Laboratory Tests

The urinary free cortisol test and the ACTH suppression test may be helpful in evaluating the HPA axis suppression.

Carcinogenesis, Mutagenesis, Impairment of Fertility

Long-term animal studies have not been performed to evaluate the carcinogenic potential of the effect of topical corticosteroids on fertility.
Studies to determine mutagenicity with prednisolone and hydrocortisone may have revealed negative results.

Pregnancy Category C

Corticosteroids are generally teratogenic in laboratory animals when administered systemically at relatively low dosage levels. The more potent corticosteroids have been shown to be teratogenic after dermal application in laboratory animals. There are no adequate and well-controlled studies in pregnant women on teratogenic effects from topically applied corticosteroids. Therefore, topical corticosteroids should be used during pregnancy only if the potential benefit justifies the potential risk to the fetus. Drugs of this class should not be used extensively on pregnant patients in large amounts or for prolonged periods of time.

Nursing Mothers

It is not known whether topical administration of corticosteroids could result in sufficient systemic absorption to produce detectable quantities in breast milk. Systemically administered corticosteroids are secreted into breast milk in quantities not likely to have a deleterious effect on the infant. Nevertheless, caution should be exercised when topical corticosteroids are administered to nursing women.

Pediatric Use

Pediatric patients may demonstrate greater susceptibility to topical corticosteroid-induced HPA axis suppression and Cushing’s syndrome than mature patients because of a larger skin surface area to body weight ratio. Hypothalamic-pituitary-adrenal (HPA) axis suppression, Cushing’s syndrome and intracranial hypertension have been reported in children receiving topical corticosteroids. Manifestations of adrenal suppression in children include linear growth retardation, delayed weight gain, low plasma cortisol levels and absence of response to ACTH stimulation. Manifestation of intracranial hypertension include bulging fontanelles, headaches and bilateral papilledema.
Administration of topical corticosteroids to children should be limited to the least amount compatible with an effective therapeutic regimen. Chronic corticosteroid therapy may interfere with the growth and development of children.

Adverse Reactions

The following local adverse reactions are reported infrequently with topical corticosteroids but may occur more frequently with the use of occlusive dressings. These reactions are listed in an approximate decreasing order of occurrence:
Burning, Itching, Irritation, Dryness, Folliculitis, Hypertrichosis, Acneiform eruptions, Hypopigmentation, Perioral dermatitis, Allergic contract dermatitis, Maceration of the skin, Secondary infection, Skin atrophy, Striae and Miliaria.

Overdosage

topically applied corticosteroids can be absorbed in sufficient amounts to produce systemic effects (see PRECAUTIONS)

DOSAGE AND ADMINISTRATION

HybriSil™ (methylprednisolone acetate 1%) silicone gel should be applied to the affected area as a thin film two or three times daily depending on the severity of the condition.
Occlusive dressings may be used for management of recalcitrant conditions. If an infection develops, the use of occlusive dressings should be discontinued and appropriate antimicrobial therapy instituted.

CAUTION

If medication accidentally gets in the eyes, wash thoroughly with water and contact a physician immediately. Keep out of the reach of children.

HOW SUPPLIED

in 30 gm bottle with pump. Prescription only.
US Patents: Pending.
Revised April 2011

Image: Bottle Label

label_cd01.jpg

Image: Carton Label

uc_CD01.jpg